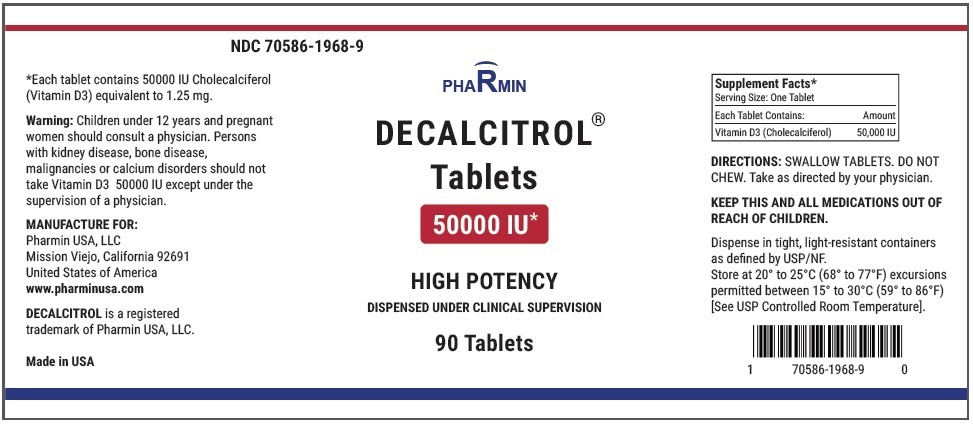 DRUG LABEL: DECALCITROL
NDC: 70586-1968 | Form: TABLET, COATED
Manufacturer: Pharmin USA, LLC
Category: other | Type: DIETARY SUPPLEMENT
Date: 20171228

ACTIVE INGREDIENTS: CHOLECALCIFEROL 50000 [iU]/1 1
INACTIVE INGREDIENTS: SILICON DIOXIDE; MAGNESIUM STEARATE; POWDERED CELLULOSE; HYPROMELLOSES

DECALCITROL® CHOLECALCIFEROL (VITAMIN D3) 1.25 mg TABLETS (50,000 Units)

HIGH POTENCY SUPPLEMENT*

*Warning: Cholecalciferol 50000 IU can be classified as either a supplement or a medication in accordance with regulations set by health ministries in different countries. In USA, Cholecalciferol 50000 IU is a high potency supplement and should be dispensed under direct clinical supervision.

DESCRIPTION

Decalcitrol (cholecalciferol-D3, Vitamin D3) is a fat-soluble high potency vitamin that helps your body absorb calcium and phosphorus.

Decalcitrol is a white, colorless crystal, insoluble in water, soluble in organic solvents, and slightly soluble in vegetable oils. It is affected by air and by light.

One Unit of vitamin D3 is equivalent to one International Unit (IU). Each Tablet, for oral administration, contains Cholecalciferol, 1.25 mg (equivalent to 50,000 USP units of Vitamin D).

Inactive Ingredients: Silica, magnesium stearate, cellulose, hydroxypropyl methylcellulose

CLINICAL PHARMACOLOGY

The in vivo synthesis of the major biologically active metabolites of vitamin D occurs in two steps. The first hydroxylation of ergocalciferol takes place in the liver (to 25-hydroxyvitamin D) and the second in the kidneys (to 1,25-dihydroxy- vitamin D). Vitamin D metabolites promote the active absorption of calcium and phosphorus by the small intestine, thus elevating serum calcium and phosphate levels sufficiently to permit bone mineralization. Vitamin D metabolites also mobilize calcium and phosphate from bone and probably increase the reabsorption of calcium and perhaps also of phosphate by the renal tubules.

There is a time lag of 10 to 24 hours between the administration of vitamin D and the initiation of its action in the body due to the necessity of synthesis of the active metabolites in the liver and kidneys.

INDICATIONS AND USAGE

Colecalciferol Tablets are essential for absorption of calcium and necessary for healthy and strong bones. Cholecalciferol Tablets are indicated for use in the treatment of hypoparathyroidism, refractory rickets, also known as vitamin D resistant rickets, and familial hypophosphatemia.

CONTRAINDICATIONS

Colecalciferol Tablets are contraindicated in patients with hypercalcemia, malabsorption syndrome, abnormal sensitivity to the toxic effects of vitamin D, and hypervitaminosis D.

WARNINGS

Hypersensitivity to vitamin D may be one etiologic factor in infants with idiopathic hypercalcemia. In these cases vitamin D must be strictly restricted. Children under 12 years and pregnant women should consult a physician. Persons with kidney disease, bone disease, malignancies or calcium disorders should not take Vitamin D3 50000 IU except under the supervision of a physician.

Keep out of the reach of children.

PRECAUTIONS

General

Vitamin D administration from fortified foods, dietary supplements, self-administered and prescription drug sources should be evaluated. Therapeutic dosage should be readjusted as soon as there is clinical improvement. Dosage levels must be individualized and great care exercised to prevent serious toxic effects. When high therapeutic doses are used progress should be followed with frequent blood calcium determinations.

Maintenance of a normal serum phosphorous level by dietary phosphate restriction and/or administration of aluminum gels as intestinal phosphate binders in those patients with hyperphosphatemia as frequently seen in renal osteodystrophy is essential to prevent metastatic calcification.

Adequate dietary calcium is necessary for clinical response to vitamin D therapy.

Drug Interactions

Mineral oil interferes with the absorption of fat-soluble vitamins, including vitamin D preparations. Administration of thiazide diuretics to hypoparathyroid patients who are concurrently being treated with vitamin D preparations may cause hypercalcemia.

Carcinogenesis, Mutagenesis, Impairment of Fertility

No long-term animal studies have been performed to evaluate the drug's potential in these areas. A judgment of the physician is required.

Pregnancy Category C

For the protection of the fetus, the use of vitamin D in excess of the recommended dietary allowance during normal pregnancy should be avoided unless, in the judgment of the physician, potential benefits in a specific, unique case outweigh the significant hazards involved. The safety in excess of 400 units of vitamin D daily during pregnancy has not been established.

Nursing Mothers

Consult with physician is required.

Pediatric Use

Pediatric doses must be individualized.

Geriatric Use

Clinical studies of Colecalciferol did not include sufficient numbers of subjects aged 65 and over to determine whether they respond differently from younger subjects. Other reported clinical experience has not identified differences in responses between the elderly and younger patients. A few published reports have suggested that the absorption of orally administered vitamin D may be attenuated in elderly compared to younger individuals. In general, dose selection for an elderly patient should be cautious, usually starting at the low end of the dosing range, reflecting the greater frequency of decreased hepatic, renal, or cardiac function, and of concomitant disease or other drug therapy. Geriatric requires seek their primary care physician before starting vitamin D therapy.

ADVERSE REACTIONS

Hypervitaminosis D is characterized by effects on the following organ system:

Renal: Impairment of renal function with polyuria, nocturia, polydipsia, hypercalciuria, reversible azotemia, hypertension, nephrocalcinosis, generalized vascular calcification, or irreversible renal insufficiency which may result in death.

CNS: Mental retardation.

Soft Tissues: Widespread calcification of the soft tissues, including the heart, blood vessels, renal tubules, and lungs.

Skeletal: Bone demineralization (osteoporosis) in adults occurs concomitantly.

Decline in the average rate of linear growth and increased mineralization of bones in infants and children (dwarfism), vague aches, stiffness, and weakness.

Gastrointestinal: Nausea, anorexia, constipation.

Metabolic: Mild acidosis, anemia, weight loss.

OVERDOSAGE

The effects of administered vitamin D can persist for two or more months after cessation of treatment.

Hypervitaminosis D is characterized by:

1. Hypercalcemia with anorexia, nausea, weakness, weight loss, vague aches and stiffness, constipation, mental retardation, anemia, and mild acidosis.
2. Impairment of renal function with polyuria, nocturia, polydipsia, hypercalciuria, reversible azotemia, hypertension, nephrocalcinosis, generalized vascular calcification, or irreversible renal insufficiency which may result in death.
3. Widespread calcification of the soft tissues, including the heart, blood vessels, renal tubules, and lungs. Bone demineralization (osteoporosis) in adults occurs concomitantly.
4. Decline in the average rate of linear growth and increased mineralization of bones in infants and children (dwarfism).

The treatment of hypervitaminosis D with hypercalcemia consists of immediate withdrawal of the vitamin, a low calcium diet, generous intake of fluids, along with symptomatic and supportive treatment. Hypercalcemic crisis with dehydration, stupor, coma, and azotemia requires more vigorous treatment. The first step should be hydration of the patient. Intravenous saline may quickly and significantly increase urinary calcium excretion. A loop diuretic (furosemide or ethacrynic acid) may be given with the saline infusion to further increase renal calcium excretion. Other reported therapeutic measures include dialysis or the administration of citrates, sulfates, phosphates, corticosteroids, EDTA (ethylenediaminetetraacetic acid), and mithramycin via appropriate regimens. With appropriate therapy, recovery is the usual outcome when no permanent damage has occurred. Deaths via renal or cardiovascular failure have been reported.

DOSAGE AND ADMINISTRATION

DOSAGE MUST BE INDIVIDUALIZED UNDER CLOSE MEDICAL SUPERVISION.

Calcium intake should be adequate. Blood calcium and phosphorus determinations must be made every 2 weeks or more frequently if necessary. X-rays of the bones should be taken every month until condition is corrected and stabilized

SWALLOW TABLETS. DO NOT CHEW. Take as directed by your physician.

Supplement Facts*; Serving Size: One Tablet
Each Tablet Contains: | Amount
Vitamin D3 (Cholecalciferol) | 50,000 IU

HOW SUPPLIED

Bottles of 90 tablets (NDC 70586-1968-9).

Store at 20°– 25°C (68°–77°F) [See USP Controlled Room Temperature].

Protect from light and moisture.

Dispense in a tight, light-resistant container as defined in the USP.

Distributed by:

Pharmin USA, LLC

Mission Viejo, California 92691

United States of America

www.pharminusa.com

DECALCITROL is a registered trademark of Pharmin USA, LLC

HEALTH CLAIM

Each tablet contains 50000 IU Vitamin D3

(Cholecalciferol) equivalent to 1.25 mg.

Vitamin D3 50,000 IU is essential for absorption of calcium and necessary for healthy bones and a healthy immune system.